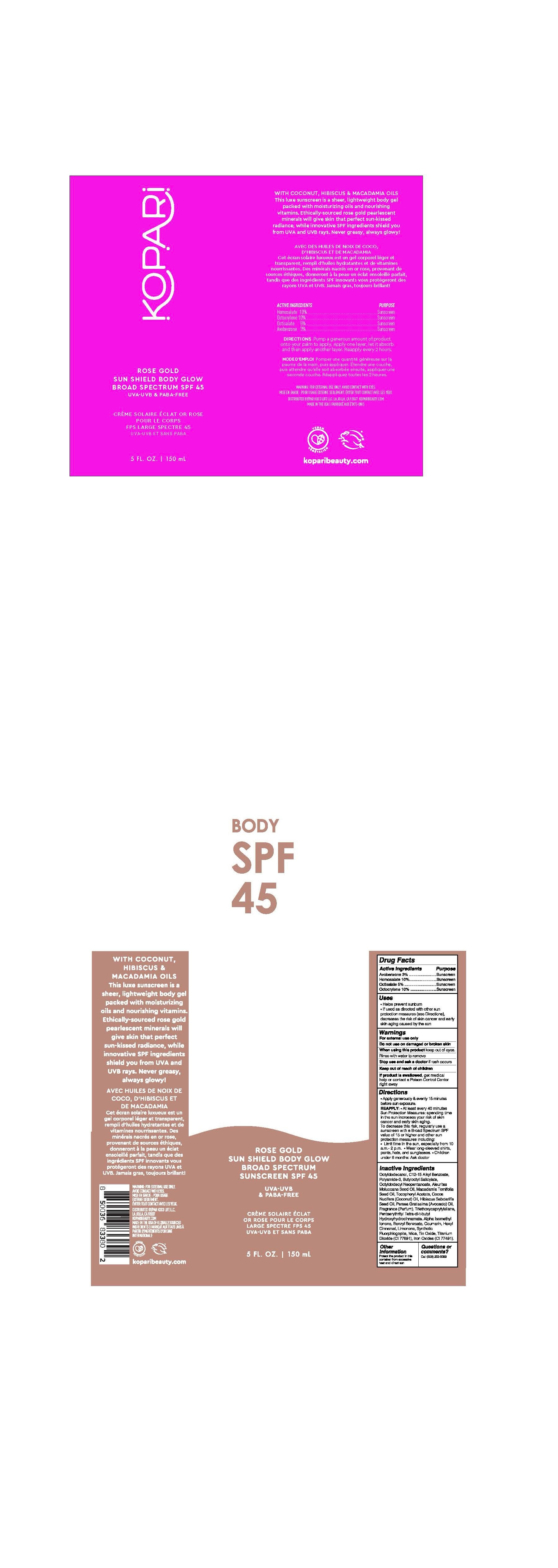 DRUG LABEL: Rose Gold Sun Shield Body Glow SPF45
NDC: 84130-002 | Form: GEL
Manufacturer: Koco Life LLC
Category: otc | Type: HUMAN OTC DRUG LABEL
Date: 20240628

ACTIVE INGREDIENTS: OCTISALATE 50 mg/1 mL; OCTOCRYLENE 100 mg/1 mL; AVOBENZONE 30 mg/1 mL; HOMOSALATE 100 mg/1 mL
INACTIVE INGREDIENTS: POLYAMIDE-3 (12000 MW); OCTYLDODECANOL; .ALPHA.-TOCOPHEROL ACETATE; KUKUI NUT OIL; COCONUT OIL; HIBISCUS SABDARIFFA SEED OIL; STANNOUS OXIDE; .ALPHA.-HEXYLCINNAMALDEHYDE; BENZYL BENZOATE; MICA; BUTYLOCTYL SALICYLATE; PENTAERYTHRITOL TETRAKIS(3-(3,5-DI-TERT-BUTYL-4-HYDROXYPHENYL)PROPIONATE); COUMARIN; TRIETHOXYCAPRYLYLSILANE; ISOMETHYL-.ALPHA.-IONONE; AVOCADO OIL; TITANIUM DIOXIDE; ALKYL (C12-15) BENZOATE; OCTYLDODECYL NEOPENTANOATE; MACADAMIA OIL; MAGNESIUM POTASSIUM ALUMINOSILICATE FLUORIDE; FERRIC OXIDE RED; LIMONENE, (+)-

Rose Gold Sun Shield Body Glow SPF45

Active ingredients

Avobenzone 3%

Homosalate 10%

Octisalate 5%

Octocrylene 10%

Purpose

Avobenzone 3% .........................Sunscreen

Homosalate 10%.........................Sunscreen

Octisalate 5% .............................Sunscreen

Octocrylene 10% ........................Sunscreen

Uses

• Helps prevent sunburn

• If used as directed with other sunprotection measures (see Directions),decreases the risk of skin cancer and early skin aging caused by the sun

Warnings

For external use only

Do not use on damaged or broken skin

When using this product keep out of eyes.
Rinse with water to remove

Stop use and ask a doctor if rash occurs

Keep out of reach of children
If product is swallowed, get medical help or contact a Poison Control Center right away

Directions

• Apply generously & evenly 15 minutes before sun exposure.

REAPPLY: • At least every 40 minutes Sun Protection Measures: spending time in the sun increases your risk of skin cancer and early skin aging. To decrease this risk, regularly use a sunscreen with a Broad Spectrum SPF value of 15 or higher and other sun protection measures including:• Limit time in the sun, especially from 10 a.m.- 2 p.m. • Wear long-sleeved shirts, pants, hats, and sunglasses. • Children under 6 months: Ask doctor

Inactive ingredients

Octyldodecanol, C12-15 Alkyl Benzoate, Polyamide-3, Butyloctyl Salicylate, Octyldodecyl Neopentanoate, Aleurites Moluccana Seed Oil, Macadamia Ternifolia Seed Oil, Tocopheryl Acetate, Cocos Nucifera (Coconut) Oil, Hibiscus Sabdariffa Seed Oil, Persea Gratissima (Avocado) Oil, Fragrance (Parfum), Triethoxycaprylylsilane, Pentaerythrityl Tetra-di-t-butyl Hydroxyhydrocinnamate, Alpha Isomethyl Ionone, Benzyl Benzoate, Coumarin, Hexyl Cinnamal, Limonene, Synthetic Fluorphlogopite, Mica, Tin Oxide, Titanium Dioxide (CI 77891), Iron Oxides (CI 77491).

Other information

Protect the product in this container from excessive heat and direct sun

Questions or comments?

Call (858) 252-0099

PACKAGE LABEL

Rose Gold

Sun Shield Body Glow

Broad Spectrum

Sunscreen SPF 45

UVA-UVB

& PABA-FREE

5 Fl. Oz. | 150 mL